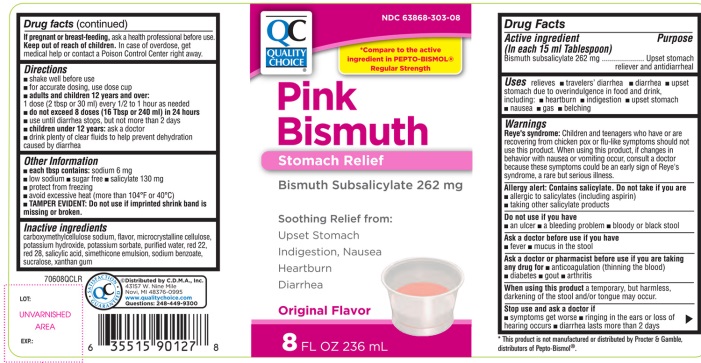 DRUG LABEL: QC Quality Choice Pink Bismuth Stomach Relief
NDC: 63868-303 | Form: SUSPENSION
Manufacturer: Chain Drug Manufacturing Assn
Category: otc | Type: HUMAN OTC DRUG LABEL
Date: 20220118

ACTIVE INGREDIENTS: Bismuth subsalicylate 262 mg/15 mL
INACTIVE INGREDIENTS: CARBOXYMETHYLCELLULOSE SODIUM, UNSPECIFIED; MICROCRYSTALLINE CELLULOSE; POTASSIUM HYDROXIDE; POTASSIUM SORBATE; WATER; D&C red no. 22; D&C red no. 28; salicylic acid; DIMETHICONE; SODIUM BENZOATE; SUCRALOSE; XANTHAN GUM

QC Quality Choice Pink Bismuth Stomach Relief Original Flavor 8 FL OZ

Drug Facts

Active ingredient (in each 15 ml Tablespoon)

Bismuth subsalicylate 262 mg

Purposes

Upset stomach reliever and antidiarrheal

Uses

relieves

- travelers’ diarrhea
- diarrhea
- upset stomach due to overindulgence in food and drink, including:
- heartburn
- indigestion
- upset stomach
- nausea
- gas
- belching

Warnings

Reye's syndrome:

Children and teenagers who have or are recovering from chicken pox or flu-like symptoms should not use this product. When using this product, if changes in behavior with nausea and vomiting occur, consult a doctor because these symptoms could be an early sign of Reye's syndrome, a rare but serious illness.

Allergy alert: Contains salicylate. Do not take if you are

- allergic to salicylates (including aspirin)
- taking other salicylate products

Do not use if you have

- an ulcer
- a bleeding problem
- bloody or black stool

Ask a doctor before use if you have

- fever
- mucus in the stool

Ask a doctor or pharmacist before use if you are taking any drug for

- anticoagulation (thinning the blood)
- diabetes
- gout
- arthritis

When using this product a temporary, but harmless, darkening of the stool and/or tongue may occur.

Stop use and ask a doctor if

- symptoms get worse
- ringing in the ears or loss of hearing occurs
- diarrhea lasts more than 2 days

PREGNANCY OR BREAST FEEDING

If pregnant or breast-feeding, ask a health professional before use.

Keep out of reach of children. In case of overdose, get medical help or contact a Poison Control Center right away.

Directions

- shake well before use
- for accurate dosing, use dose cup
- adults and children 12 years and over:
  1 dose (2 tbsp or 30 ml) every ½ to 1 hour as needed
- do not exceed 8 doses (16 tbsp or 240 ml) in 24 hours
- use until diarrhea stops but not more than 2 days
- children under 12 years: ask a doctor
- drink plenty of clear fluids to help prevent dehydration caused by diarrhea

Other information

- each tbsp contains: sodium 6 mg
  - low sodium
  - sugar free
  - salicylate 130 mg
  - protect from freezing
  - avoid excessive heat (more than 104°F or 40°C)
- TAMPER EVIDENT: Do not use if imprinted shrink band is missing or broken.

Inactive ingredients

carboxymethylcellulose sodium, flavor, microcrystalline cellulose, potassium hydroxide ,potassium sorbate, purified water, red 22,red 28, salicylic acid, simethicone emulsion, sodium benzoate ,sucralose, xanthan gum

PRINCIPAL DISPLAY PANEL - 236 mL Bottle Label

QC

Quality Choice®

NDC 63868-303-08

*Compare to the active ingredient in PEPTO-BISMOL® Regular strength

PINK BISMUTH

Stomach Relief

Bismuth Subsalicylate 262mg

Soothing Relief from:

Upset Stomach
Indigestion, Nausea
Heartburn

- Diarrhea
NaN Original Flavor

8 FL OZ (236 mL)

QC SATISFACTION GUARANTEED

©Distributed by C.D.M.A., Inc.

43157 W. Nine Mile

Novi, MI 48376-0995

www.qualitychoice.com

Questions: 248-449-9300

*This product is not manufactured or distributed by Procter & Gamble, distributors of Pepto-Bismol®.